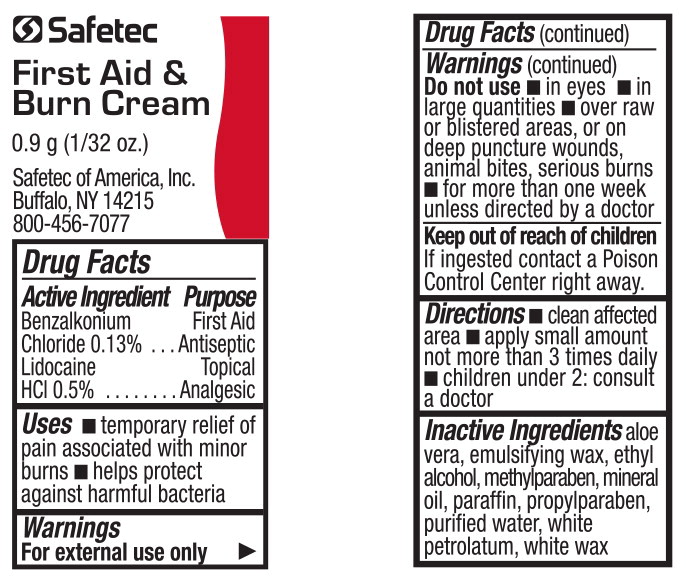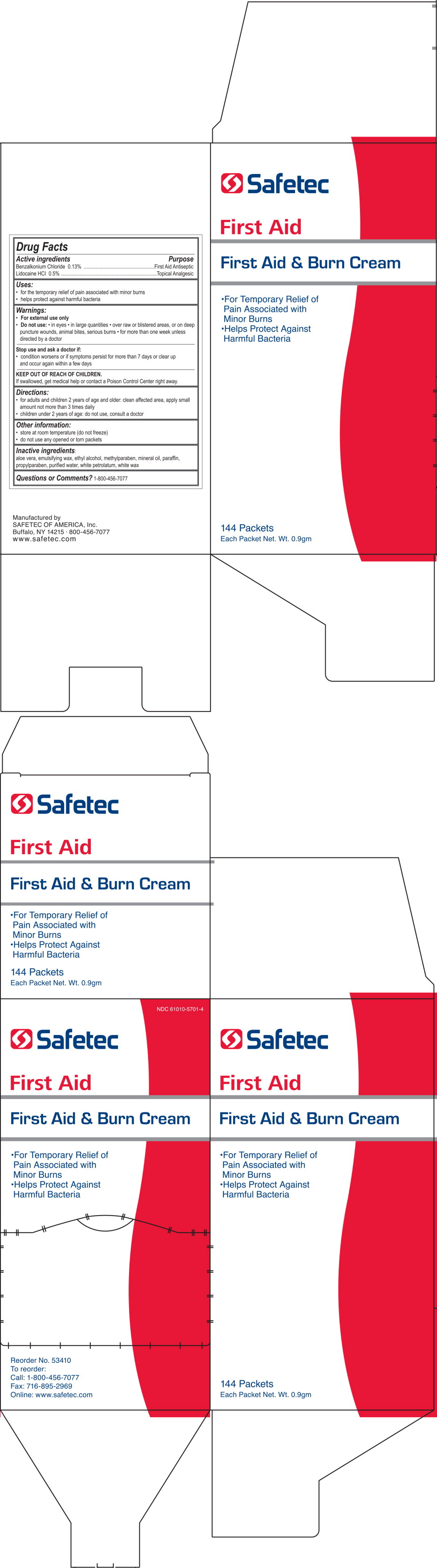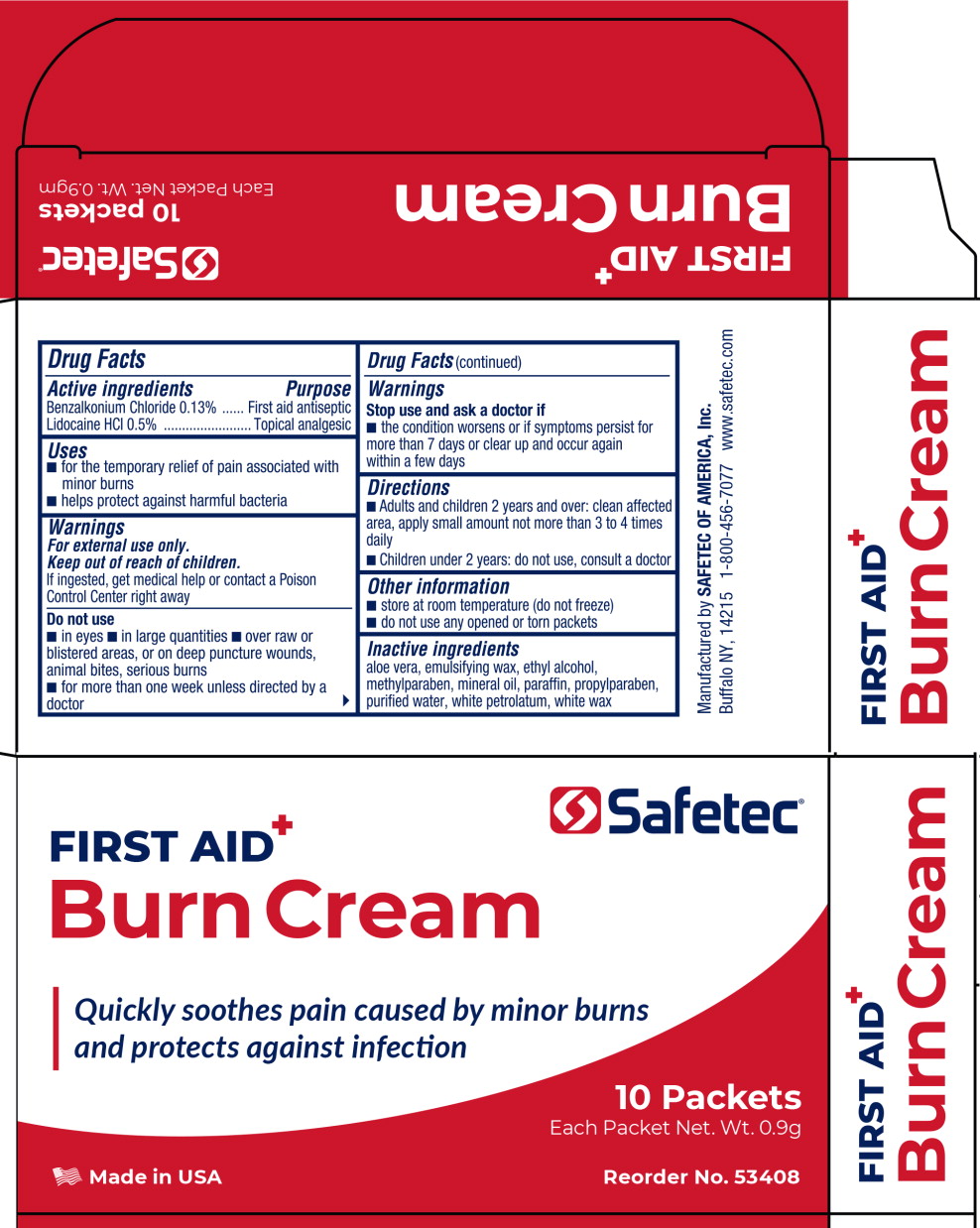 DRUG LABEL: First Aid and Burn
NDC: 61010-5701 | Form: CREAM
Manufacturer: Safetec of America, Inc.
Category: otc | Type: HUMAN OTC DRUG LABEL
Date: 20240207

ACTIVE INGREDIENTS: BENZALKONIUM CHLORIDE 1.3 mg/1 g; LIDOCAINE HYDROCHLORIDE 5 mg/1 g
INACTIVE INGREDIENTS: ALOE VERA LEAF; ALCOHOL; METHYLPARABEN; MINERAL OIL; PARAFFIN; PROPYLPARABEN; WATER; PETROLATUM; WHITE WAX

61010-5701, First Aid and Burn Cream

Drug Facts

Active Ingredients

Benzalkonium Chloride 0.13%

Lidocaine HCl 0.5%

Purpose

First Aid Antiseptic

Topical Analgesic

Uses

- temporary relief of pain associated with minor burns
- helps protect against harmful bacteria

Warnings

For external use only

Do not use

- in eyes
- in large quantities
- over raw or blistered areas, or on deep puncture wounds, animal bites, serious burns
- for more than one week unless directed by a doctor

Keep out of reach of children.

If ingested contact a Poison Control Center right away.

Directions

- clean affected area
- apply small amount not more than 3 times daily
- children under 2: consult a doctor

Inactive ingredients

aloe vera, emulsifying wax, ethyl alcohol, methylparaben, mineral oil, paraffin, propylparaben, purified water, white petrolatum, white wax

PRINCIPAL DISPLAY PANEL – 0.9 gram packet

NDC 61010-5701-03

Safetec

First Aid &
Burn Cream

0.9 g (1/32 oz.)

Safetec of America, Inc.
Buffalo, NY 14215
800-456-7077

PRINCIPAL DISPLAY PANEL – 144 count box

NDC 61010-5701-4

Safetec

First Aid

First Aid & Burn Cream

- For Temporary Relief of
  Pain Associated with
  Minor Burns
- Helps Protect Against
  Harmful Bacteria

Reorder No. 53410
To reorder:
Call: 1-800-456-7077
Fax: 716-895-2969
Online: www.safetec.com

Principal Display Panel – 10 Packet Box Label

Safetec®

FIRST AID

Burn Cream

Quickly soothes pain caused by minor burns
and protects against infection

10 Packets

Each Packet Net. Wt. 0.9g

Made in USA

Reorder No. 53408